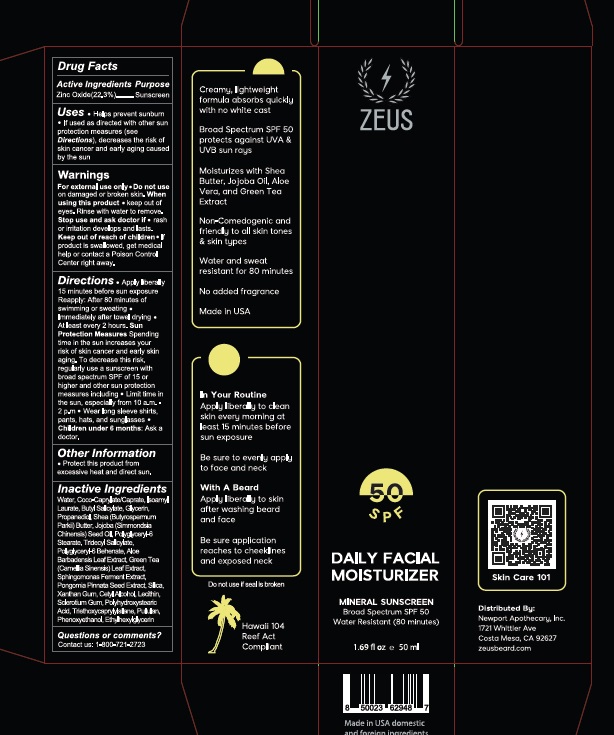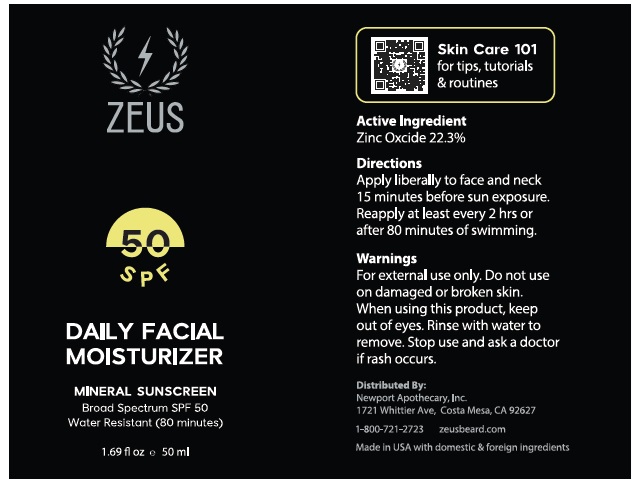 DRUG LABEL: ZEUS
NDC: 84697-001 | Form: CREAM
Manufacturer: NEWPORT APOTHECARY, INC
Category: otc | Type: HUMAN OTC DRUG LABEL
Date: 20251112

ACTIVE INGREDIENTS: ZINC OXIDE 22.3 g/100 mL
INACTIVE INGREDIENTS: WATER; COCOYL CAPRYLOCAPRATE; ISOAMYL LAURATE; BUTYL SALICYLATE; GLYCERIN; PROPANEDIOL; JOJOBA OIL; SHEA BUTTER; POLYGLYCERYL-6 STEARATE; TRIDECYL SALICYLATE; POLYGLYCERYL-6 BEHENATE; ALOE VERA LEAF; GREEN TEA LEAF; PONGAMIA PINNATA SEED; XANTHAN GUM; CETYL ALCOHOL; SILICON DIOXIDE; SOYBEAN LECITHIN; BETASIZOFIRAN; POLYHYDROXYSTEARIC ACID STEARATE; PULLULAN; PHENOXYETHANOL; ETHYLHEXYLGLYCERIN; TRIETHOXYCAPRYLYLSILANE

Active Ingredient Purpose

ZINC OXIDE 22.3% SUNSCREEN

Uses

- HELPS PREVENT SUNBURN
- IF USED AS DIRECTED WITH OTHER SUN PROTECTION MEASURES (SEE DIRECTIONS), DECREASES THE RISK OF SKIN CANCER AND EARLY AGING CAUSED BY THE SUN

Warnings

- For external use only
- Do not use ondamaged or broken skin. When using this product
- Keep out of eyes. Rinse with water to remove. Stop use and ask doctor if
- rash or irritation develops and lasts. Keep out of reach of children
- If product is swallowed, get medical help of contact a Poison Control Center right away.

Directions

- APPLY LIBERALLY 15 MINUTES BEFORE SUN EXPOSURE REAPPLY: AFTER 80 MINUTES OF SWIMMING OR SWEATING
- IMMEDIATELY AFTER TOWEL DRYING
- AT LEAST EVERY 2 HOURS.
- SUN PROTECTION MEASURESSPENDING TIME IN THE SUN INCREASES YOUR RISK OF SKIN CANCER AND EARLY SKIN AGING. TO DECREASE THIS RISK, REGULARLY USE A SUNSCREEN WITH BROAD SPECTRUM SPF OF 15 OR HIGHER AND OTHER SUN PROTECTION MEASURES INCLUDING
- LIMIT TIME IN THE SUN, ESPECIALLY FROM 10 A.M.-2 P.M.
- WEAR LONG SLEEVE SHIRTS, PANTS, HATS, AND SUNGLASSES
- CHILDREN UNDER 6 MONTHS: ASK A DOCTOR

Other information

PROTECT THIS PRODUCT FROM EXCESSIVE HEAT AND DIRECT SUN.

Inactive Ingredients

WATER, COCO-CAPYLATE/CAPRATE (COCOYL CAPRYLOCAPRATE), ISOAMYL LAURATE, BUTYL SALICYLATE, GLYCERIN, PROPANEDIOL, BUTYROSPERMUM PARKII (SHEA BUTTER), SIMMONDSIA CHINENSIS (JOJOBA OIL),POLYGLYCERYL-6 STEARATE, TRIDECYL SALICYLATE, POLYGLYCERYL-6 BEHENATE, ALOE BARBADENSIS LEAF EXTRACT (ALOE VERA LEAF), CAMELLIA SINENSIS (GREEN TEA LEAF), SPHINGOMONAS FERMENT EXTRACT, PONGOMIA PINNATA SEED, Silica, XANTHAN GUM, CETYL ALCOHOL, LECITHIN, SCLEROTIUM GUM (BETASIZOFIRAN), POLYHYDROXYSTEARIC ACID, TRIETHOXYCAPRYLYLSILANE, PULLULAN, PHENOXYETHANOL, ETHYLHEXYLGLYCERIN

Questions or comments?

Contact us : 1-800-721-2723